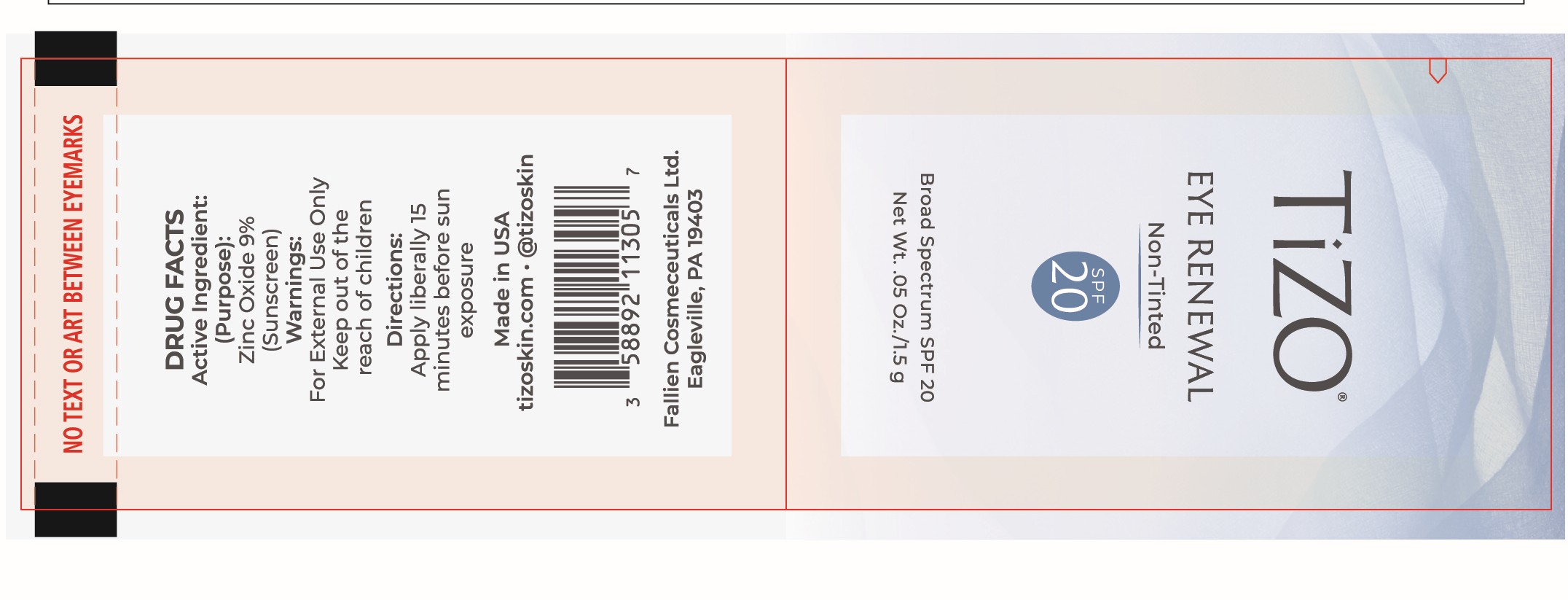 DRUG LABEL: TiZO Eye Renewal SPF 20 (Non-Tinted)
NDC: 58892-113 | Form: CREAM
Manufacturer: Fallien Cosmeceuticals, LTD
Category: otc | Type: HUMAN OTC DRUG LABEL
Date: 20250203

ACTIVE INGREDIENTS: ZINC OXIDE 90 mg/1 g
INACTIVE INGREDIENTS: TETRAHEXYLDECYL ASCORBATE; PEG-10 DIMETHICONE (600 CST); SAMBUCUS NIGRA FLOWER; DIMETHICONOL (2000 CST); POLYSORBATE 20; SACCHAROMYCES CEREVISIAE; CAPRYLHYDROXAMIC ACID; ALPHA-TOCOPHEROL ACETATE; PALMITOYL TETRAPEPTIDE-7; GLYCERIN; ISOHEXADECANE; PALMITOYL TRIPEPTIDE-1; SILANETRIOL; LAURYL PEG/PPG-18/18 METHICONE; BUTYLENE GLYCOL; CORALLINA OFFICINALIS; DIMETHICONE CROSSPOLYMER; WATER; DIMETHICONE/VINYL DIMETHICONE CROSSPOLYMER (SOFT PARTICLE); HYDROGEN DIMETHICONE (20 CST); ISODODECANE; CYCLOHEXASILOXANE; CYCLOPENTASILOXANE; CARBOMER; CAPRYLYL GLYCOL; CAFFEINE; UNDARIA PINNATIFIDA

Active Ingredient:

Zinc Oxide 9%

Purpose:

Sunscreen

Directions:

Apply liberally 15 minutes before sun exposure.

Warning:

For external use only. Keep out of the reach of children.

Warning and Directions:

For external use only. Keep out of the reach of children. Apply liberally 15 minutes before sun exposure.

INACTIVE INGREDIENT

Butylene Glycol, Caffeine, Carbomer, Caprylhydroxamic Acid, Caprylyl Glycol, Corallina Officinalis Extract, Cyclohexasiloxane, Cyclopentasiloxane, Dimethicone Crosspolymer, Dimethicone/Vinyl Dimethicone Crosspolymer, Dimethiconol, Glycerin, Hydrogen Dimethicone, Isododecane, Isohexadecane, Lauryl PEG/PPG-18/18 Methicone, Palmitoyl Tripeptide-1, Palmitoyl Tetrapeptide-7, PEG-10 Dimethicone, Polysorbate 20, Saccharomyces/Selenium Ferment, Sambucus Nigra Flower Extract, Siloxanetriol Alginate, Tetrahexyldecyl Ascorbate, Tocopheryl Acetate, Undaria Pinnatifida Extract, Water

Warning:

Keep out of the reach of children.